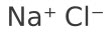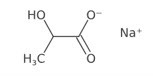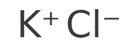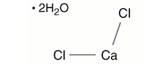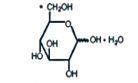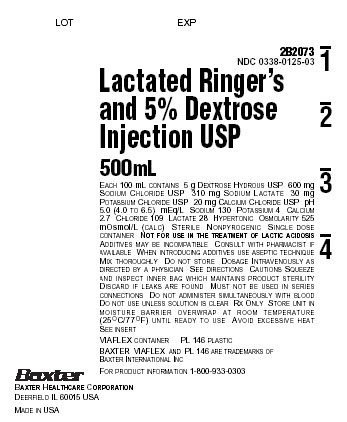 DRUG LABEL: Lactated Ringers and Dextrose
NDC: 0338-0125 | Form: INJECTION, SOLUTION
Manufacturer: Baxter Healthcare Corporation
Category: prescription | Type: HUMAN PRESCRIPTION DRUG LABEL
Date: 20251029

ACTIVE INGREDIENTS: DEXTROSE MONOHYDRATE 5 g/100 mL; SODIUM CHLORIDE 600 mg/100 mL; SODIUM LACTATE 310 mg/100 mL; POTASSIUM CHLORIDE 30 mg/100 mL; CALCIUM CHLORIDE 20 mg/100 mL
INACTIVE INGREDIENTS: WATER

HIGHLIGHTS OF PRESCRIBING INFORMATION

These highlights do not include all the information needed to use LACTATED RINGER’S AND DEXTROSE (5%) INJECTION safely and effectively. See full prescribing information for LACTATED RINGER’S AND DEXTROSE (5%) INJECTION.
LACTATED RINGER’S AND DEXTROSE injection for intravenous use
Initial U.S. Approval: 1971

RECENT MAJOR CHANGES

Dosage and Administration (2.1, 2.2, 2.3, 2.4) 10/2025
Contraindications (4) 10/2025
Warnings and Precautions (5.1, 5.2, 5.3, 5.4, 5.5, 5.6, 5.7, 5.8, 5.9, 5.10, 5.11) 10/2025

1 INDICATIONS AND USAGE

Lactated Ringer’s and Dextrose (5%) Injection is indicated for use as a source of water, electrolytes, and calories or as an alkalinizing agent in adults and pediatric patients. (1)

2 DOSAGE AND ADMINISTRATION

- The recommended dosage and duration are based on the patient’s age, weight, clinical condition, and concomitant therapy. (2.1)
- To reduce the risk of air embolism, adhere to the preparation instructions. (2.2, 5.2)
- Lactated Ringer’s and Dextrose (5%) Injection is for intravenous use. (2.3)
- Use a peripheral vein to administer if the final dextrose concentration is 5% or less, and the osmolarity is less than 900 mOsm/L. (2.3)
- Consider using a central vein to administer hypertonic solutions with osmolarity of 900 mOsm/L or more to avoid venous irritation, including phlebitis. (2.3)
- Do not administer Lactated Ringer’s and Dextrose (5%) Injection simultaneously with ceftriaxone in neonates (28 days of age or younger) due to serious risks. (2.4)
- See full prescribing information for information dosage considerations, preparation, administration, and drug incompatibilities. (2)

3 DOSAGE FORMS AND STRENGTHS

Injection: Lactated Ringer’s and Dextrose (5%) Injection, USP packaged in single-dose Viaflex flexible containers: 500 mL and 1,000 mL. (3)

4 CONTRAINDICATIONS

- Concomitant treatment with ceftriaxone in neonates (28 days of age or younger). (4)
- Patients with known hypersensitivity to any of the components of Lactated Ringer’s and Dextrose (5%) Injection. (4)
- Patients with clinically significant hyperglycemia. (4)

5 WARNINGS AND PRECAUTIONS

- Serious Risks with Inappropriate Use with Ceftriaxone: Deaths have occurred in neonates (28 days of age or younger) who received concomitant intravenous calcium-containing solutions with ceftriaxone. In patients older than 28 days, ceftriaxone and Lactated Ringer’s and Dextrose (5%) Injection may be administered sequentially if the infusion lines are thoroughly flushed between infusions. (4, 5.1, 8.4)
- Air Embolism: Use a non-vented infusion set or close the vent on a vented set and use a dedicated line without any connections. Pressure infusion is not recommended to increase flow rates, but if necessary, remove all air from the bag prior to initiating infusion. (5.2)
- Hypersensitivity Reactions: Stop the Lactated Ringer’s and Dextrose (5%) Injection infusion immediately if signs or symptoms of a hypersensitivity reaction develop. (5.3)
- Potassium Imbalances, Hyponatremia, Neonatal Hypoglycemia, Hyperglycemia and Hyperosmolar Hyperglycemic State, Hypercalcemia, Fluid Overload, Acid-Base Imbalances, Interference with Interpretation of Serum Lactate Levels in Patients with Severe Metabolic Acidosis: See Full Prescribing Information for risk management recommendations. (5.4, 5.5, 5.6, 5.7, 5.8, 5.9, 5.10, 5.11)

6 ADVERSE REACTIONS

Common adverse reactions include infusion site reactions and symptoms of hypersensitivity reactions (e.g., pruritus, dyspnea, urticaria, rash, cough). (6)

To report SUSPECTED ADVERSE REACTIONS, contact Baxter Healthcare at 1-866-888-2472 or FDA at 1-800-FDA-1088 or www.fda.gov/medwatch.

7 DRUG INTERACTIONS

- Drugs that Affect Electrolyte and/or Fluid Balance: Avoid concomitant use. If concomitant use cannot be avoided, closely monitor electrolyte concentrations and fluid balance. (7.1)
- Lithium: Avoid concomitant use. If concomitant use is unavoidable, monitor serum lithium concentrations more frequently. (7.2)
- Digoxin: Consider reducing the volume or rate of Lactated Ringer’s and Dextrose (5%) Injection due to the increased risk of digoxin toxicity with calcium-containing solutions. (7.3)
- Drugs with pH-Dependent Renal Elimination: Renal clearance of acidic drugs may be increased. In contrast, renal clearance of alkaline drugs may be decreased. (7.4)

8 USE IN SPECIFIC POPULATIONS

- Closely monitor plasma electrolyte concentrations in young pediatric patients with immature kidney function. (8.4)
- Neonates are at increased risk of developing hypo- or hyperglycemia. Closely monitor to ensure adequate glycemic control. (8.4)
- Geriatric patients are more likely to have decreased renal function. Consider monitoring renal function and starting the infusion at the low end of the dosing range. (8.5)
- Avoid in patients with severe renal impairment. (8.6)
- Patients with severe hepatic impairment may have impaired lactate metabolism. Closely monitor serum lactate levels and acid-base status. (8.7)

FULL PRESCRIBING INFORMATION

1 INDICATIONS AND USAGE

Lactated Ringer’s and Dextrose (5%) Injection is indicated for use as a source of water, electrolytes, and calories or as an alkalinizing agent in adults and pediatric patients.

2 DOSAGE AND ADMINISTRATION

2.1 Dosage Considerations

The recommended dosage and duration of Lactated Ringer’s and Dextrose (5%) Injection is based on the patient’s age, weight, clinical condition, and concomitant therapy. Evaluate the patient’s clinical status and monitor changes in blood glucose and electrolyte concentrations, especially during prolonged use of Lactated Ringer’s and Dextrose (5%) Injection to optimize clinical status.

2.2 Important Preparation Instructions

Visually inspect the Lactated Ringer’s and Dextrose (5%) Injection solution for particulate matter and discoloration. Do not administer Lactated Ringer’s and Dextrose (5%) Injection unless the solution is clear and the container seals are intact.

If additives are determined to be compatible with Lactated Ringer’s and Dextrose (5%) Injection then using aseptic technique, mix thoroughly; do not store solutions containing additives. After mixing, do not use if there is discoloration or formation of precipitates.

To reduce the risk of air embolism, adhere to the following preparation instructions for Lactated Ringer’s and Dextrose (5%) Injection [see Warnings and Precautions (5.2)]:

- Use a non-vented infusion set or close the vent on a vented set.
- Use a dedicated line without any connections (do not connect flexible containers in series).
- The use of pressure infusion is not recommended as a method to increase flow rates. However, if pressure infusion is required, ensure that any air within the bag is fully evacuated prior to initiation of infusion.
- If using a pumping device to administer Lactated Ringer’s and Dextrose (5%) Injection, turn off the pump before the container is empty.

Preparation Instructions

1. Tear overwrap downside at slit and remove solution container.
2. Visually inspect the container.
  1. If the outlet port protector is damaged, detached, or not present, discard container as solution path sterility may be impaired.
  2. Some opacity of the plastic due to moisture absorption during the sterilization process may be observed. This is normal and does not affect the solution quality or safety. The opacity will diminish gradually.
3. Check for minute leaks by squeezing inner bag firmly. If leaks are found, discard solution as sterility may be impaired.
4. If supplemental medication is desired, follow directions below [see Dosage and Administration (2.3)].

Preparation for Administration

1. Suspend container from eyelet support.
2. Remove protector from outlet port at bottom of container.
3. Attach administration set according to its accompanying directions.

2.3 Important Administration Instructions

Lactated Ringer’s and Dextrose (5%) Injection is for intravenous use.

Use immediately after removing the overwrap. Discard the unused portion.

- Use a peripheral vein to administer Lactated Ringer’s and Dextrose (5%) Injection if the final dextrose concentration is 5% or less, and the osmolarity is less than 900 mOsm/L.
- Consider using a central vein to administer hypertonic solutions with osmolarity of 900 mOsm/L or more to avoid venous irritation [see Warnings and Precautions (5.7)].
  Some additives may be incompatible [see Dosage and Administration (2.4) and Contraindications (4)].

To Add Medication Before Solution Administration

1. Prepare medication site.
2. Using syringe with 19 to 22 gauge needle, puncture resealable medication port and inject.
3. Mix solution and medication thoroughly. For high density medication such as potassium chloride, squeeze ports while ports are upright and mix thoroughly.

To Add Medication During Solution Administration

1. Close clamp on the set.
2. Prepare medication site.
3. Using syringe with 19 to 22 gauge needle, puncture resealable medication port and inject.
4. Remove container from IV pole and/or turn to an upright position.
5. Evacuate both ports by squeezing them while container is in the upright position.
6. Mix solution and medication thoroughly.
7. Return container to in use position and continue administration.

2.4 Drug Incompatibilities

Do not administer Lactated Ringer’s and Dextrose (5%) Injection simultaneously with ceftriaxone in neonates (28 days of age or younger) due to serious risks [see Contraindications (4) and Warnings and Precautions (5.1)]. However, in patients older than 28 days, ceftriaxone and Lactated Ringer’s and Dextrose (5%) Injection may be administered sequentially if the infusion lines are thoroughly flushed between infusions with a compatible fluid [see Warnings and Precautions (5.1)].

Do not administer Lactated Ringer’s and Dextrose (5%) Injection simultaneously with citrate anticoagulated/preserved blood through the same administration set because of the likelihood of coagulation precipitated by the calcium content of Lactated Ringer’s and Dextrose (5%) Injection.

3 DOSAGE FORMS AND STRENGTHS

Injection: Lactated Ringer’s and Dextrose (5%) Injection, USP as a clear, sterile, and nonpyrogenic solution packaged in single-dose VIAFLEX plastic containers: 500 mL, 1000 mL

4 CONTRAINDICATIONS

Lactated Ringer’s and Dextrose (5%) Injection is contraindicated in:

- Neonates (28 days of age or younger) who are receiving concomitant treatment with ceftriaxone, even if separate infusion lines are used, due to the risk of fatal ceftriaxone-calcium salt precipitation in the neonate’s bloodstream [see Warnings and Precautions (5.1) and Specific Populations (8.4)].
- Patients with known hypersensitivity to any of the components of Lactated Ringer’s and Dextrose (5%) Injection [see Warnings and Precautions (5.3)].
- Patients with clinically significant hyperglycemia [see Warnings and Precautions (5.7)].

5 WARNINGS AND PRECAUTIONS

5.1 Serious Risk with Concomitant Use with Ceftriaxone

Precipitation of ceftriaxone-calcium can occur when ceftriaxone is mixed with calcium-containing solutions, such as Lactated Ringer’s and Dextrose (5%) Injection, in the same intravenous administration line. Deaths have occurred in neonates (28 days of age or younger) who received concomitant intravenous calcium-containing solutions with ceftriaxone resulting from calcium-ceftriaxone precipitates in the lungs and kidneys, even when separate infusion lines were used.

Lactated Ringer’s and Dextrose (5%) Injection is contraindicated in neonates who receive ceftriaxone [see Contraindications (4), Use in Specific Populations (8.4)]. However, in patients older than 28 days, ceftriaxone and Lactated Ringer’s and Dextrose (5%) Injection may be administered sequentially if the infusion lines are thoroughly flushed between infusions with a compatible fluid.

5.2 Air Embolism

Cases of air embolism have been reported with pressurized administration of intravenous fluids. Air embolism may result in stroke, organ ischemia and/or infarction, and death.

Use a non-vented infusion set or close the vent on a vented set and use a dedicated line without any connections.

If administration is controlled by a pumping device, care must be taken to discontinue the pumping action before the container is empty.

Pressure infusion is not recommended to increase flow rates, but if necessary, ensure all air is removed from the bag before infusion.

Refrain from applying excessive pressure (>300mmHg) causing distortion to the container such as wringing or twisting. Such handling could result in breakage of the container [see Dosage and Administration (2.2)].

5.3 Hypersensitivity Reactions

Hypersensitivity reactions, including anaphylaxis and angioedema, have been reported with Lactated Ringer’s solution. Stop the Lactated Ringer’s and Dextrose (5%) Injection infusion immediately and treat patient accordingly if signs or symptoms of a hypersensitivity reaction develop. Initiate appropriate treatment as clinically indicated.

5.4 Potassium Imbalances

Hyperkalemia

Potassium-containing solutions, including Lactated Ringer’s and Dextrose (5%) Injection, may increase the risk of hyperkalemia. This risk is increased in patients predisposed to hyperkalemia including those with severe renal impairment, acute dehydration, extensive tissue injury or burns, heart failure, or in those using concomitant drugs that are associated with hyperkalemia.

Avoid use of Lactated Ringer’s and Dextrose (5%) Injection in patients with, or at increased risk for, hyperkalemia. If use cannot be avoided in these patients, closely monitor serum potassium concentrations.

Hypokalemia

The potassium concentration in Lactated Ringer’s and Dextrose (5%) Injection is similar to the concentration in plasma. It is insufficient to normalize the serum potassium in patients with severe hypokalemia.

5.5 Hyponatremia

Lactated Ringer’s and Dextrose (5%) Injection may cause hyponatremia. Hyponatremia can lead to acute hyponatremic encephalopathy characterized by headache, nausea, seizures, lethargy and vomiting. The risk of hospital-acquired hyponatremia is increased in younger pediatric patients, geriatric patients, patients treated with diuretics, patients with cardiac or pulmonary failure, or patients with the syndrome of inappropriate antidiuretic hormone (SIADH) (e.g., postoperative patients, patients concomitantly treated with arginine vasopressin analogs, or certain antiepileptic, psychotropic, or cytotoxic drugs) [see Drug Interactions (7.1), Use in Specific Populations (8.4)]. Avoid Lactated Ringer’s and Dextrose (5%) Injection in patients with or at risk for hyponatremia. If use cannot be avoided in these patients, closely monitor serum sodium concentrations.

Rapid correction of hyponatremia may result in serious neurologic complications such as osmotic demyelination syndrome (ODS). To avoid complications, monitor serum sodium and chloride concentrations, fluid status, acid-base balance, and neurologic status.

5.6 Neonatal Hypoglycemia

Neonates, especially preterm neonates with low birth weight, are at increased risk of developing hypoglycemia. Closely monitor blood glucose concentration during treatment with intravenous dextrose solutions to ensure adequate glycemic control in order to avoid potential long-term adverse effects.

5.7 Hyperglycemia and Hyperosmolar Hyperglycemic State

Administration of solutions containing dextrose and lactate in patients with impaired glucose tolerance including those with diabetes mellitus may worsen hyperglycemia. Hyperglycemia is associated with an increase in serum osmolality, which can result in hypovolemia and electrolyte imbalances due to osmotic diuresis.

Patients with underlying central nervous system disease or renal impairment who receive dextrose infusions may be at greater risk of developing hyperosmolar hyperglycemic state.

While using Lactated Ringer’s and Dextrose (5%) Injection, closely monitor blood glucose concentrations and treat hyperglycemia to maintain glucose concentrations within normal limits. Anti-diabetic drugs may need to be started or dosages of these drugs may need to be increased to maintain optimal blood glucose concentrations.

5.8 Hypercalcemia

Lactated Ringer’s and Dextrose (5%) Injection contains calcium salts and may cause hypercalcemia. Avoid administration of Lactated Ringer’s and Dextrose (5%) Injection in patients with hypercalcemia, those with calcium-containing renal calculi or history of such calculi, those with conditions predisposing to hypercalcemia, or those treated with concomitant thiazide diuretics or vitamin D.

5.9 Fluid Overload

Depending on the administered volume and the infusion rate, administration of Lactated Ringer’s and Dextrose (5%) Injection can cause fluid overload, including pulmonary edema.

Avoid Lactated Ringer’s and Dextrose (5%) Injection in patients at risk for fluid and/or solute overload including patients with severe renal impairment. If use cannot be avoided in these patients, monitor fluid balance, electrolyte concentrations and acid base balance, especially during prolonged use.

5.10 Acid/Base Imbalances

Because lactate is metabolized to bicarbonate, administration of Lactated Ringer’s and Dextrose (5%) Injection may result in, or worsen, metabolic alkalosis. Closely monitor the acid-base balance in patients with, or at risk of, alkalosis.

In patients with severe hepatic impairment, decreased lactate metabolism may result in worsening anion gap metabolic acidosis. Avoid Lactated Ringer’s and Dextrose (5%) Injection in patients with severe hepatic impairment. If use cannot be avoided in these patients, closely monitor serum bicarbonate levels.

5.11 Interference of Lactated Ringer’s and Dextrose (5%) Injection with Interpretation of Serum Lactate Levels in Patients with Severe Metabolic Acidosis

Administration of Lactated Ringer’s and Dextrose (5%) Injection may result in interference with the interpretation of serum lactate levels in patients with severe metabolic acidosis, including lactic acidosis [see Drug Interactions (7.5)].

6 ADVERSE REACTIONS

The following serious adverse reactions are discussed in greater detail in other sections of the labeling:

- Serious Risk with Concomitant Use with Ceftriaxone [see Warnings and Precautions (5.1)]
- Air Embolism [see Warnings and Precautions (5.2)]
- Hypersensitivity Reactions [see Warnings and Precautions (5.3)]
- Potassium Imbalances [see Warnings and Precautions (5.4)]
- Hyponatremia [see Warnings and Precautions (5.5)]
- Neonatal Hypoglycemia [see Warnings and Precautions (5.6)]
- Hyperglycemia and Hyperosmolar Hyperglycemic State [see Warnings and Precautions (5.7)]
- Hypercalcemia [see Warnings and Precautions (5.8)]
- Fluid Overload [see Warnings and Precautions (5.9)]
- Acid/Base Imbalances [see Warnings and Precautions (5.10)]

The following adverse reactions have been identified during post approval use of Lactated Ringer’s products. Because these reactions are reported voluntarily from a population of uncertain size, it is not always possible to reliably estimate their frequency or establish a causal relationship to drug exposure:

General Disorders and Administration Site Conditions:
Phlebitis, extravasation, infusion site inflammation, infusion site swelling, infusion site rash, infusion site pruritus, infusion site erythema, infusion site pain, infusion site burning and infusion site hypoaesthesia.
Hypersensitivity Reactions and Infusion Reactions:
Angioedema, chest pain/discomfort, bradycardia or tachycardia, hypotension, respiratory distress, bronchospasm, dyspnea, cough, urticaria, rash, pruritus, erythema, flushing, throat irritation, paresthesia, oral hypoesthesia, dysgeusia, nausea, anxiety, pyrexia, and headache, laryngeal edema, sneezing, and injection site infection.
Metabolism and Nutrition Disorders:
Hyperkalemia, hyponatremia, and hypervolemia.
Nervous System Disorders:
Hyponatremic encephalopathy.

7 DRUG INTERACTIONS

7.1 Drugs that Affect Electrolyte and/or Fluid Balance

Hyperkalemia

Administration of Lactated Ringer’s and Dextrose (5%) Injection to patients concomitantly treated or recently treated with drugs that are associated with hyperkalemia increases the risk of severe and potentially fatal hyperkalemia, especially in the presence of other hyperkalemia risk factors. Avoid use of Lactated Ringer’s and Dextrose (5%) Injection in patients receiving drugs that are associated with hyperkalemia (e.g., potassium-sparing diuretics, ACE inhibitors, angiotensin II receptor antagonists, or calcineurin inhibitors). If concomitant use cannot be avoided, closely monitor serum potassium concentrations during concomitant use [see Warnings and Precautions (5.4)].

Hyponatremia

Administration of Lactated Ringer’s and Dextrose (5%) Injection to patients treated concomitantly with drugs associated with hyponatremia may increase the risk of developing hyponatremia. These drugs include diuretics and those that cause SIADH (e.g., arginine vasopressin analogs, certain antiepileptic, psychotropic, or cytotoxic drugs). Avoid use of Lactated Ringer’s and Dextrose (5%) Injection in patients receiving such drugs. If use cannot be avoided, closely monitor serum sodium concentrations during concomitant use [see Warnings and Precautions (5.5)].

Hypercalcemia

Avoid the use of Lactated Ringer’s and Dextrose (5%)Injection in patients treated with thiazide diuretics or vitamin D because these drugs can increase the risk of hypercalcemia. If use cannot be avoided, closely monitor serum calcium concentrations during concomitant use [see Warnings and Precautions (5.8)].

Hypernatremia and Fluid Retention

Administration of Lactated Ringer’s and Dextrose (5%) Injection to patients treated concomitantly with drugs associated with sodium and fluid retention (e.g., corticosteroids or corticotropin) may increase the risk of hypernatremia and volume overload. Avoid use of Lactated Ringer’s and Dextrose (5%) Injection in patients receiving such drugs. If use cannot be avoided, closely monitor serum electrolytes, fluid balance, and acid-base balance during concomitant use.

7.2 Lithium

Renal sodium and lithium clearance may be increased during concomitant use of Lactated Ringer’s and Dextrose (5%) Injection and lithium and may result in decreased lithium concentrations. Avoid use of Lactated Ringer’s and Dextrose (5%)Injection in patients receiving lithium. If use cannot be avoided, increase the frequency of monitoring of serum lithium concentrations during concomitant use.

7.3 Digoxin

Administration of calcium via use of Lactated Ringer’s and Dextrose (5%) Injection may increase digoxin’s effects and lead to digoxin toxicity including serious or fatal cardiac arrhythmias. In digoxin-treated patients, consider reducing the volume and/or rate of Lactated Ringer’s and Dextrose (5%) Injection administration.

7.4 Drugs with pH-Dependent Renal Elimination

Due to the alkalinizing action of lactate (formation of bicarbonate), Lactated Ringer’s and Dextrose (5%) Injection may interfere with the elimination of drugs with pH-dependent renal elimination. Renal clearance of alkaline drugs may be decreased. In contrast, renal clearance of acidic drugs may be increased.

7.5 Interference of Lactated Ringer’s and Dextrose (5%) Injection with Interpretation of Serum Lactate Levels in Patients with Severe Metabolic Acidosis

Because administration of Lactated Ringer’s and Dextrose (5%) Injection may interfere with the interpretation of serum lactate levels in patients with severe metabolic acidosis, including lactic acidosis, assessment of the patient’s clinical status should not solely rely on the measurement of serum lactate.

8 USE IN SPECIFIC POPULATIONS

8.1 Pregnancy

Risk Summary

Lactated Ringer’s as a source of water and electrolytes and Dextrose (5%) Injection have been used for decades during labor and delivery. Although there are a few case reports that describe adverse effects of dextrose use and no reports of use of Lactated Ringer’s in other stages of pregnancy, exposure to Lactated Ringer’s and Dextrose (5%) Injection during pregnancy in general is not expected to cause major birth defects, miscarriage, or adverse maternal or fetal outcomes. Animal reproduction studies have not been conducted with this drug.

The background risk of major birth defects and miscarriage for the indicated population is unknown. All pregnancies have a background risk of birth defect, loss, or other adverse outcomes. In the U.S. general population, the estimated background risk of major birth defects and miscarriage in clinically recognized pregnancies is 2 to 4% and 15 to 20%, respectively. Therefore, it is not known whether Lactated Ringer’s and Dextrose (5%) Injection can cause fetal harm when administered to a pregnant woman. Lactated Ringer’s and Dextrose (5%) Injection should be given during pregnancy only if the potential benefit justifies the potential risk to the fetus.

8.2 Lactation

Risk Summary

Lactated Ringer’s as a source of water and electrolytes and Dextrose (5%) Injection have been used for decades and is not expected to cause harm to a breastfed infant. There are no data on the presence of Lactated Ringer’s and Dextrose (5%) Injection in human Imilk, the effects on the breastfed infant, or the effects on milk production. The developmental and health benefits of breastfeeding should be considered along with the mother’s clinical need for Lactated Ringer’s and Dextrose (5%) Injection and any potential adverse effects on the breastfed infant from Lactated Ringer’s and Dextrose (5%) Injection or from the underlying maternal condition.

8.4 Pediatric Use

Lactated Ringer’s and Dextrose (5%) Injection is contraindicated in neonates (28 days of age or younger) who are receiving ceftriaxone due to reported deaths that occurred when neonates received ceftriaxone and intravenous calcium-containing solutions concomitantly [see Warnings and Precautions (5.1)].

The safety and effectiveness of Lactated Ringer’s Injection for use as a source of water, electrolytes, and calories or as an alkalinizing agent have been established in pediatric patients of all ages, including neonates.

Closely monitor plasma electrolyte concentrations in young pediatric patients with immature kidney function who may have decreased ability to maintain fluid and electrolyte balance [see Warnings and Precautions (5.4, 5.5, 5.8, 5.9)]. Administration of a lactate-containing intravenous solution, including Lactated Ringer’s and Dextrose (5%) Injection to pediatric patients should account for liver and kidney maturation (the kidney function affects the biotransformation and renal excretion of lactate) [see Warnings and Precautions (5.9)]. Pediatric patients are at increased risk for developing hyponatremic encephalopathy [see Warnings and Precautions (5.5)].

Neonates, especially preterm neonates with low birth weight, are at increased risk of developing hypo- or hyperglycemia and therefore need close monitoring during treatment with intravenous glucose solutions including Lactated Ringer’s and Dextrose (5%) Injection to ensure adequate glycemic control to avoid potential long-term adverse reactions [see Warnings and Precautions (5.6, 5.7)]. In very low birth weight neonates, excessive or rapid administration of Lactated Ringer’s and Dextrose (5%) Injection may result in increased serum osmolality and risk of intracranial hemorrhage.

8.5 Geriatric Use

Geriatric patients treated with Lactated Ringer’s and Dextrose (5%) Injection are at increased risk of developing electrolyte imbalances. Lactated Ringer’s and Dextrose (5%) Injection is substantially excreted by the kidney, and the risk of adverse reactions to Lactated Ringer’s and Dextrose (5%) Injection may be greater in patients with renal impairment than in patients with normal renal function. Because geriatric patients are more likely to have decreased renal function, consider monitoring renal function in geriatric patients and consider starting the infusion at the low end of the dosing range.

8.6 Renal Impairment

Administration of Lactated Ringer’s and Dextrose (5%) Injection to patients with or at risk of severe renal impairment, may result in hyperkalemia and/or fluid overload [see Warnings and Precautions (5.4, 5.7, 5.9)]. Avoid Lactated Ringer’s and Dextrose (5%) Injection in patients with severe renal impairment. If use cannot be avoided in such patients, monitor for development of these adverse reactions.

8.7 Hepatic Impairment

In patients with severe hepatic impairment, lactate metabolism may be impaired, and Lactated Ringer’s and Dextrose (5%) Injection may not produce alkalinization. Closely monitor serum lactate levels and acid-base status in such patients.

10 OVERDOSAGE

Excessive administration of Lactated Ringer’s and Dextrose (5%) Injection can cause:

- Hyperkalemia and hypernatremia, especially in patients with severe renal impairment.
- Fluid overload (which can lead to pulmonary and/or peripheral edema).
- Hyperglycemia, hyperosmolarity, and osmotic diuresis, dehydration, and electrolyte loss.
- Metabolic alkalosis with or without hypokalemia.
- Loss of bicarbonate with an acidifying effect.
- Hypercalcemia.

Overdose interventions include Lactated Ringer’s and Dextrose (5%) Injection discontinuation, treatment of electrolyte imbalances, treatment of hyperglycemia, and close monitoring of fluid balance, electrolyte concentrations, and acid-base balance [see Warnings and Precautions (5.4, 5.5, 5.6, 5.7, 5.9, 5.10)].

11 DESCRIPTION

Lactated Ringer’s and Dextrose (5%) Injection, USP is a sterile, nonpyrogenic solution for fluid and electrolyte replenishment and caloric supply in a single-dose container for intravenous administration. Composition, osmolarity, pH, ionic concentration and caloric content are shown in Table 1. Dextrose is derived from corn.

Table 1
 | Size (mL) | Composition (g/L) |  |  |  |  | [Normal physiologic osmolarity range is approximately 280 to 310 mOsmol/L.] Osmolarity (mOsmol/L) (calc) | pH | Ionic Concentration (mEq/L) |  |  |  |  | Caloric Content (kcal/L)
 | Size (mL) | Dextrose, USP | Sodium Chloride, USP | Sodium Lactate | Potassium Chloride, USP | Calcium Chloride, USP | [Normal physiologic osmolarity range is approximately 280 to 310 mOsmol/L.] Osmolarity (mOsmol/L) (calc) | pH | Sodium | Potassium | Calcium | Chloride | Lactate | Caloric Content (kcal/L)
Lactated Ringer’s and Dextrose (5%) Injection, USP | 500; 1000 | 50 | 6 | 3.1 | 0.3 | 0.2 | 525 | 5.0; (4.0 to; 6.5) | 130 | 4 | 2.7 | 109 | 28 | 180

The chemical name, structural formula, and molecular weight of the active ingredients are shown in Table 2.

Table 2
Chemical Name | Structural Formula | Molecular Weight
Sodium Chloride, USP |  | 58.44
Sodium Lactate |  | 112.06
Potassium Chloride, USP |  | 74.55
Calcium Chloride, USP |  | 147.02
Dextrose, USP |  | 198.17

The VIAFLEX plastic container is fabricated from polyvinyl chloride (PL 146 Plastic). Small amounts of its chemical components (e.g., di-2-ethylhexyl phthalate [DEHP]) may leach out within the expiration period. Animal tests, USP biological tests for plastic containers, and tissue culture toxicity studies have demonstrated that the container meets safety requirements. The container is overwrapped to provide protection from the physical environment and an additional moisture barrier.

12 CLINICAL PHARMACOLOGY

12.1 Mechanism of Action

Lactated Ringer’s and Dextrose (5%) Injection is a source of water, electrolytes, and calories, and produces an alkalinizing effect.

- Sodium, the major cation of the extracellular fluid, functions primarily in the control of water distribution, fluid balance, and osmotic pressure of body fluids. Sodium is also associated with chloride and bicarbonate in the regulation of the acid-base equilibrium of body fluid.
- Potassium, the principal cation of intracellular fluid, participates in carbohydrate utilization and protein synthesis and is critical in the regulation of nerve conduction and muscle contraction, particularly in the heart.
- Chloride, the major extracellular anion, closely follows the metabolism of sodium, and changes in the acid-base balance of the body are reflected by changes in the chloride concentration.
- Calcium, an important cation, provides the framework of bones and teeth in the form of calcium phosphate and calcium carbonate. In the ionized form, calcium is essential for the functional mechanism of the clotting of blood, normal cardiac function, and regulation of neuromuscular irritability.
- Sodium lactate provides sodium and lactate ions. The lactate anion is in equilibrium with pyruvate and has an alkalinizing effect resulting from simultaneous removal by the liver of lactate and hydrogen ions. The sodium ion combines with bicarbonate ion produced from carbon dioxide of the body and thus retains bicarbonate to combat metabolic acidosis (bicarbonate deficiency).
- Dextrose provides a source of calories. Dextrose may decrease losses of body protein and nitrogen, promotes glycogen deposition and decreases or prevents ketosis if sufficient doses are provided.

12.2 Pharmacodynamics

The exposure-response relationship and time course of pharmacodynamic response for the safety and effectiveness of Lactated Ringer’s and Dextrose (5%) Injection have not been fully characterized.

12.3 Pharmacokinetics

Elimination

Metabolism/Excretion

Potassium: Normally about 80 to 90% of the potassium intake is excreted in the urine; the remainder is excreted in feces and to a smaller extent, in perspiration.

Sodium and Chloride: The distribution and excretion of sodium (Na+) and chloride (Cl−) are largely under the control of the kidney which maintains a balance between intake and output.

Lactate: In the liver, lactate is metabolized to carbon dioxide and water by oxidative metabolism and consumption of hydrogen cations.

Dextrose: Dextrose injected parenterally undergoes oxidation to carbon dioxide and water.

13 NONCLINICAL TOXICOLOGY

13.1 Carcinogenesis, Mutagenesis, Impairment of Fertility

Carcinogenicity, genetic toxicology, and animal fertility studies have not been conducted with Lactated Ringer’s and Dextrose (5%) Injection.

16 HOW SUPPLIED/STORAGE AND HANDLING

How Supplied
Lactated Ringer’s and Dextrose (5%) Injection, USP is supplied as a clear solution in single-dose VIAFLEX plastic containers as follows:

Code | Size (mL) | NDC
2B2073 | 500 | NDC 0338-0125-03
2B2074 | 1000 | NDC 0338-0125-04

Storage and Handling
Store at room temperature (recommended 25°C/77°F).

Brief exposure up to 40°C (104°F) does not adversely affect the product. Exposure to heat should be minimized. Avoid excessive heat.

Baxter Healthcare Corporation
Deerfield, IL 60015 USA
Baxter, PL 146, and Viaflex are trademarks of Baxter International Inc. or its subsidiaries.

07-19-00-9426

PACKAGE/LABEL PRINCIPAL DISPLAY PANEL

Container Label

Container Label

LOT

EXP

2B2073

NDC 0338-0125-03

Lactated Ringer's
and 5% Dextrose
Injection USP

500mL

EACH 100 mL CONTAINS 5 g DEXTROSE HYDROUS USP 600 mg
SODIUM CHLORIDE USP 310 mg SODIUM LACTATE 30 mg
POTASSIUM CHLORIDE USP 20 mg CALCIUM CHLORIDE USP pH
5.0 (4.0 TO 6.5) mEq/L SODIUM 130 POTASSIUM 4 CALCIUM
2.7 CHLORIDE 109 LACTATE 28 HYPERTONIC OSMOLARITY 525
mOsmol/L (CALC) STERILE NONPYROGENIC SINGLE DOSE
CONTAINER NOT FOR USE IN THE TREATMENT OF LACTIC ACIDOSIS
ADDITIVES MAY BE INCOMPATIBLE CONSULT WITH PHARMACIST IF
AVAILABLE WHEN INTRODUCING ADDITIVES USE ASEPTIC TECHNIQUE
MIX THOROUGHLY DO NOT STORE DOSAGE INTRAVENEOUSLY AS
DIRECTED BY A PHYSICIAN SEE DIRECTIONS CAUTIONS SQUEEZE
AND INSPECT INNER BAG WHICH MAINTAINS PRODUCT STERILITY
DISCARD IF LEAKS ARE FOUND MUST NOT BE USED IN SERIES
CONNECTIONS DO NOT ADMINISTER SIMULTANEOUSLY WITH BLOOD
DO NOT USE UNLESS SOLUTION IS CLEAR Rx ONLY STORE UNIT IN
MOISTURE BARRIER OVERWRAP AT ROOM TEMPERATURE
(25°C/77°F) UNTIL READY TO USE AVOID EXCESSIVE HEAT
SEE INSERT

VIAFLEX CONTAINER PL 146 PLASTIC

BAXTER VIAFLEX AND PL 146 ARE TRADEMARKS OF
BAXTER INTERNATIONAL INC

FOR PRODUCT INFORMATION 1-800-933-0303

Baxter Logo
BAXTER HEALTHCARE CORPORATION
DEERFIELD IL 60015 USA

MADE IN USA